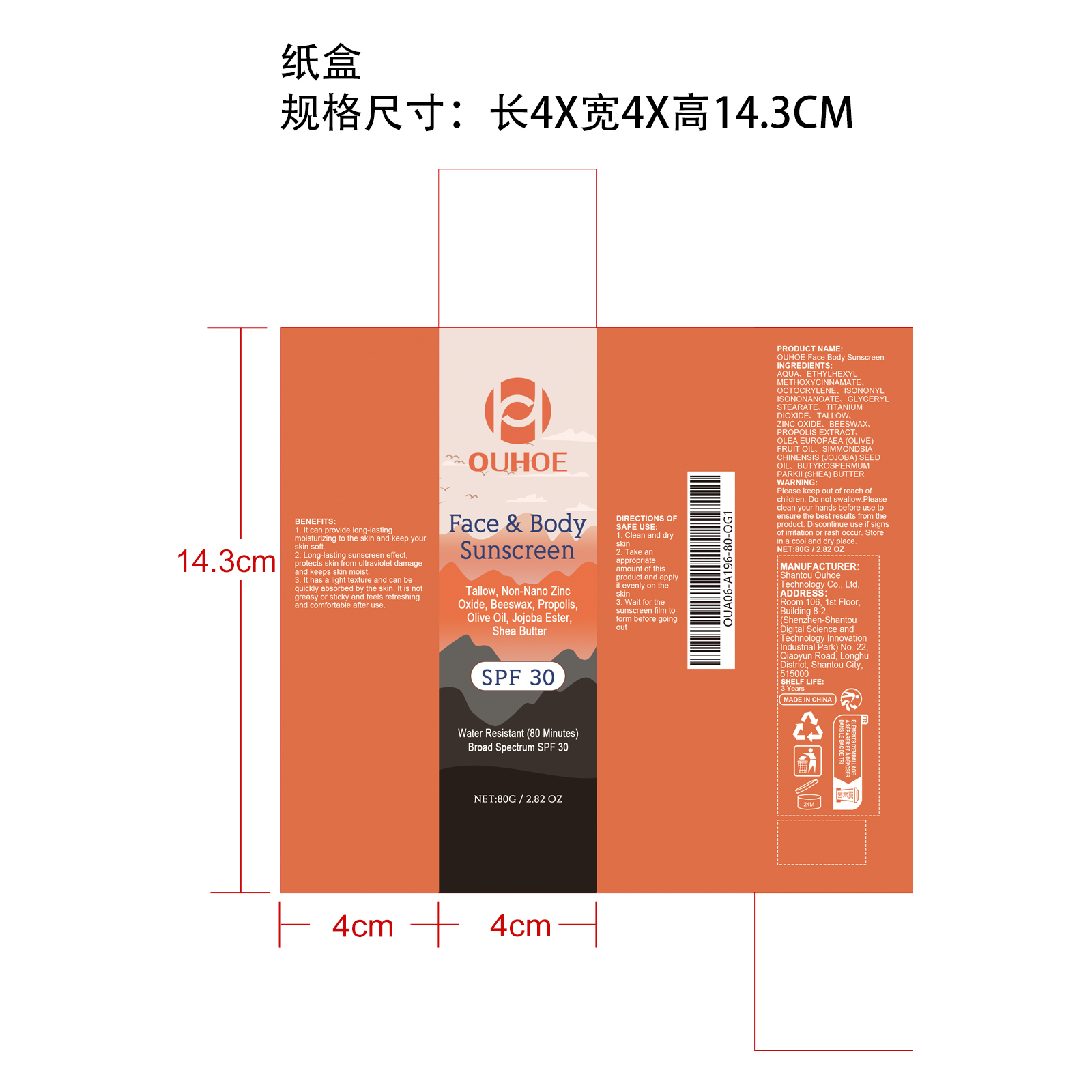 DRUG LABEL: OUHOE Face Body Sunscreen
NDC: 85163-017 | Form: CREAM
Manufacturer: Shantou Ouhoe Technology Co., Ltd.
Category: otc | Type: HUMAN OTC DRUG LABEL
Date: 20251226

ACTIVE INGREDIENTS: SIMMONDSIA CHINENSIS (JOJOBA) SEED OIL 0.016 mg/80 mg; PROPOLIS WAX 0.016 mg/80 mg; OLEA EUROPAEA (OLIVE) FRUIT OIL 0.016 mg/80 mg; BEESWAX 0.016 mg/80 mg; BUTYROSPERMUM PARKII (SHEA) BUTTER 0.016 mg/80 mg
INACTIVE INGREDIENTS: GLYCERYL STEARATE 1.2 mg/80 mg; ZINC OXIDE 0.016 mg/80 mg; ISONONYL ISONONANOATE 3.2 mg/80 mg; TITANIUM DIOXIDE 0.8 mg/80 mg; AQUA 65.088 mg/80 mg; ETHYLHEXYL METHOXYCINNAMATE 4.8 mg/80 mg; OCTOCRYLENE 4.8 mg/80 mg; TALLOW 0.016 mg/80 mg

ACTIVE INGREDIENT

BEESWAX、PROPOLIS EXTRACT、OLEA EUROPAEA (OLIVE) FRUIT OIL、SIMMONDSIA CHINENSIS (JOJOBA) SEED OIL、BUTYROSPERMUM PARKII (SHEA) BUTTER

PURPOSE

1. lt can provide long-lasting moistunzing to the skin and keep your skin soft.
2. Long-lasting sunscreen effect,protects skin from ultraviolet damage and keeps skin moist.
3. It has a light texture and can be quickly absorbed by the skin.It is not greasy or sticky and feels refreshing and comfortable after use.

WHEN USING

1. Clean and dry skin
2. Take an appropriate amount of this product and apply
it evenly on the skin
3. Wait for the sunscreen film to form before going out

WARNINGS

Please keep out of reach of children. Do not swallow.Please clean your hands before use to ensure the best results from the product. Discontinue use if signs of irritation or rash occur. Store in a cool and dry place.

DO NOT USE

Discontinue use if signs of irritation or rash occur.

STOP USE

Discontinue use if signs of irritation or rash occur.

KEEP OUT OF REACH OF CHILDREN

Please keep out of reach of children. Do not swallow.

STORAGE AND HANDLING

Store in a cool and dry place.

INACTIVE INGREDIENT

AQUA、ETHYLHEXYL METHOXYCINNAMATE、OCTOCRYLENE、ISONONYL ISONONANOATE、GLYCERYL STEARATE、TITANIUM DIOXIDE、TALLOW、ZINC OXIDE

INDICATIONS AND USAGE

1. Clean and dry skin
2. Take an appropriate amount of this product and apply
it evenly on the skin
3. Wait for the sunscreen film to form before going out

DOSAGE AND ADMINISTRATION

1. Clean and dry skin
2. Take an appropriate amount of this product and apply
it evenly on the skin
3. Wait for the sunscreen film to form before going out